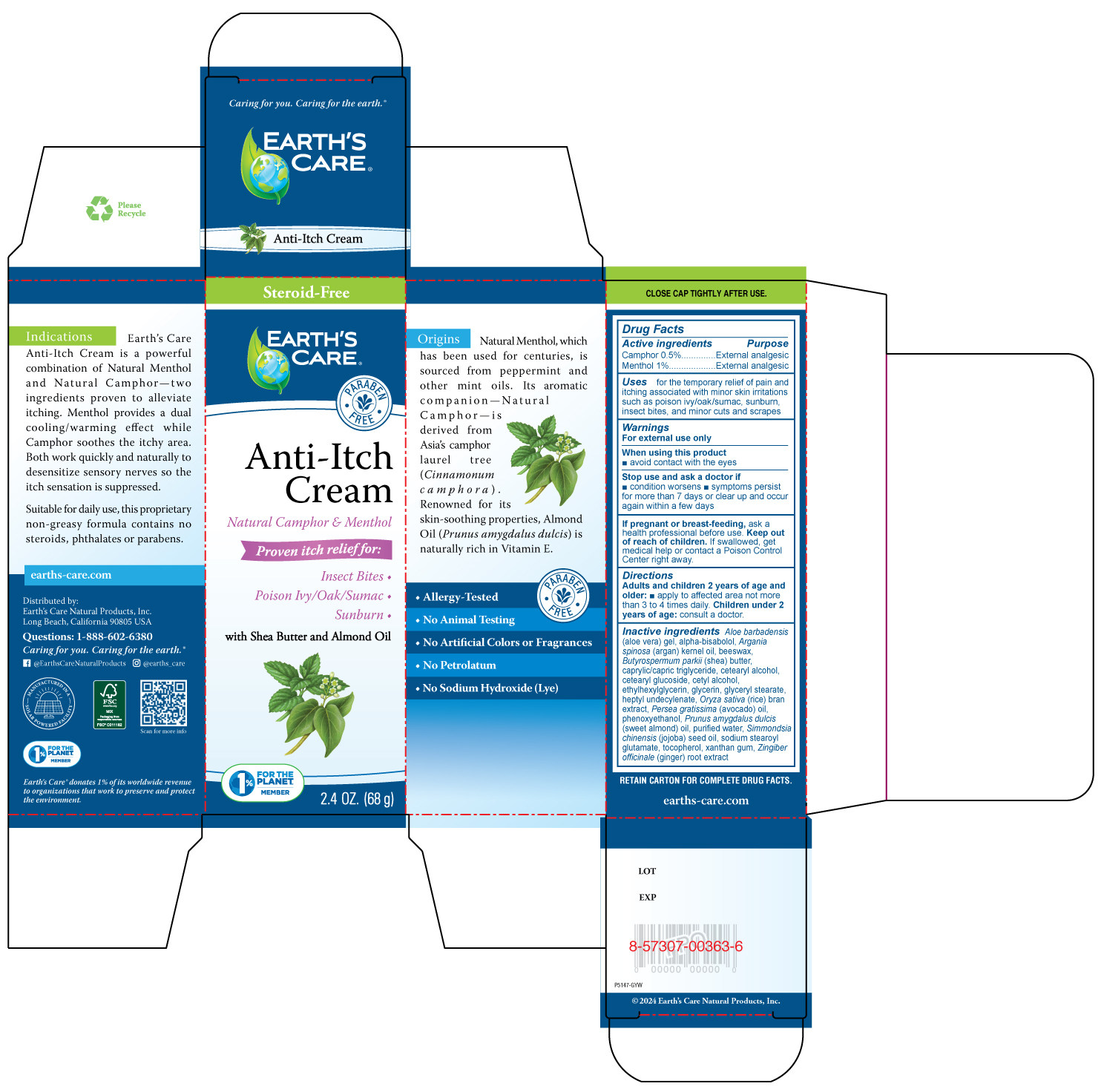 DRUG LABEL: EARTHS CARE ANTI-ITCH
NDC: 24286-1558 | Form: CREAM
Manufacturer: DLC Laboratories, Inc.
Category: otc | Type: HUMAN OTC DRUG LABEL
Date: 20260113

ACTIVE INGREDIENTS: CAMPHOR (NATURAL) 0.5 g/100 g; MENTHOL, UNSPECIFIED FORM 1 g/100 g
INACTIVE INGREDIENTS: GINGER; BEESWAX; JOJOBA OIL; AVOCADO OIL; ALOE VERA LEAF JUICE; ALMOND OIL; TOCOPHEROL; ARGAN OIL; GLYCERYL STEARATE; CETEARYL ALCOHOL; SHEA BUTTER; CETEARYL GLUCOSIDE; CETYL ALCOHOL; GLYCERIN; HEPTYL UNDECYLENATE; RICE BRAN; PHENOXYETHANOL; WATER; SODIUM STEAROYL GLUTAMATE; XANTHAN GUM; CAPRYLIC/CAPRIC TRIGLYCERIDE; .ALPHA.-BISABOLOL, (+)-; ETHYLHEXYLGLYCERIN

EARTH'S CARE™ANTI-ITCH CREAM

Drug Facts

ACTIVE INGREDIENT

Active ingredients | Purpose
Camphor 0.5% | External analgesic
Menthol 1% | External analgesic

Uses

for the temporary relief of pain and itching associated with minor skin irritations such as poison ivy/oak/sumac, sunburn, insect bites, and minor cuts and scrapes

Warnings

For external use only

When using this product

- avoid contact with the eyes

Stop use and ask a doctor if

- condition worsens
- symptoms persist for more than 7 days or clear up and occur again within a few days

PREGNANCY OR BREAST FEEDING

If pregnant or breast-feeding,ask a health professional before use.

Keep out of reach of children.If swallowed, get medical help or contact a Poison Control Center right away.

Directions

Adults and children 2 years of age and older:

- apply to affected area not more than 3 to 4 times daily. Children under 2 years of age:consult a doctor.

Inactive ingredients

beeswax, Butyrospermum parkii(shea) butter, cetearyl glucoside, cetyl alcohol, citric acid, glycerin, glyceryl stearate, heptyl undecylenate, hydrogenated castor oil, Oryza sativa(rice) bran extract, phenoxyethanol, potassium sorbate, Prunus amygdalus dulcis(sweet almond) oil, purified water, sodium stearoyl glutamate, sodium stearoyl lactylate, stearic acid, xanthan gum

Distributed by:
Earth's Care Natural Products, Inc.
Long Beach, California 90805 USA

PRINCIPAL DISPLAY PANEL - 68 g Tube Box

Steroid-Free

EARTH'S
CARE™

PARABEN
• FREE •

Anti-Itch
Cream

Natural Camphor & Menthol

Proven itch relief for:

Insect Bites •

Poison Ivy/Oak/Sumac •

Sunburn •

with Shea Butter and Almond Oil

1%
FOR THE
PLANET
MEMBER

2.4 OZ. (68 g)